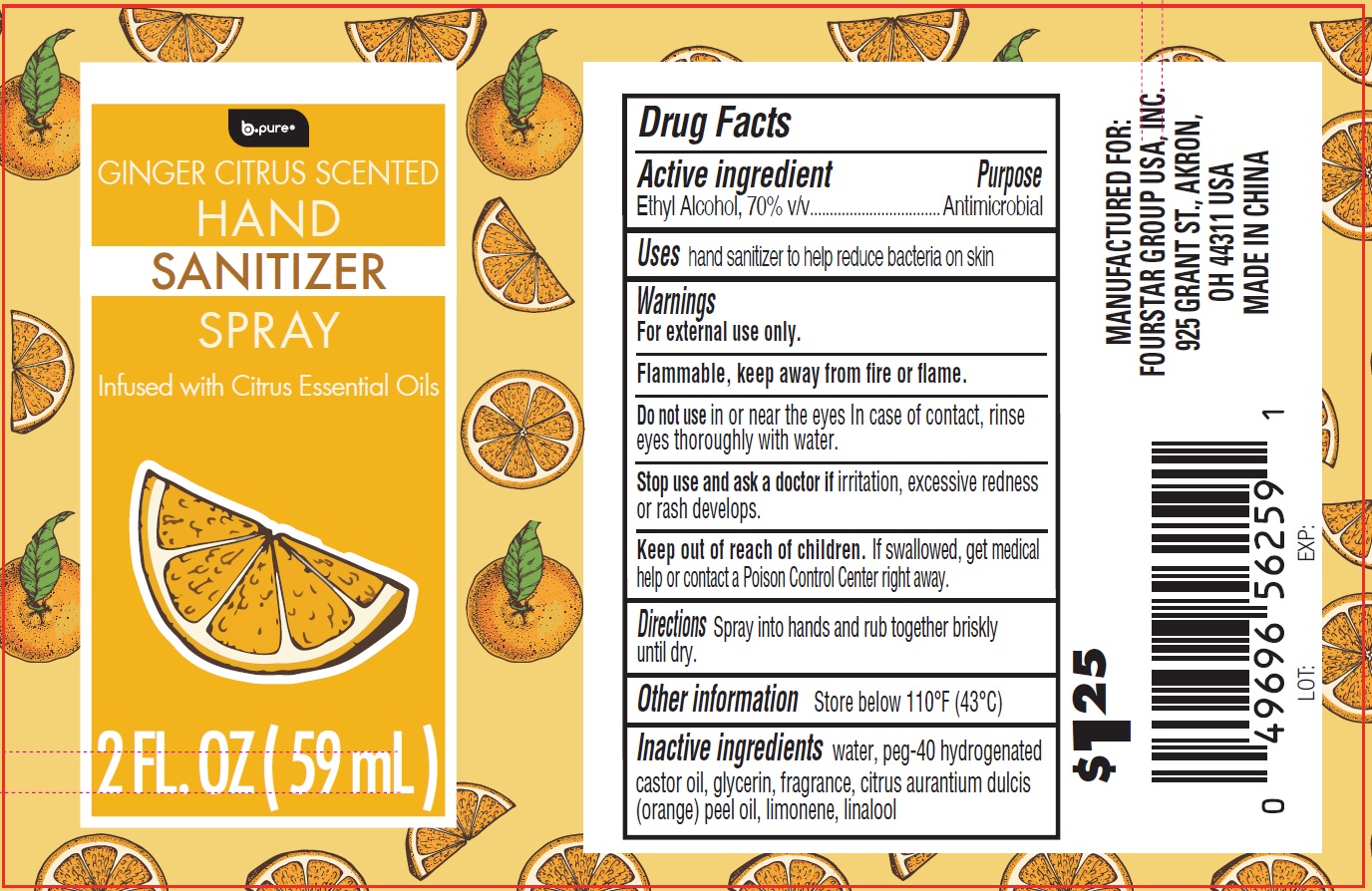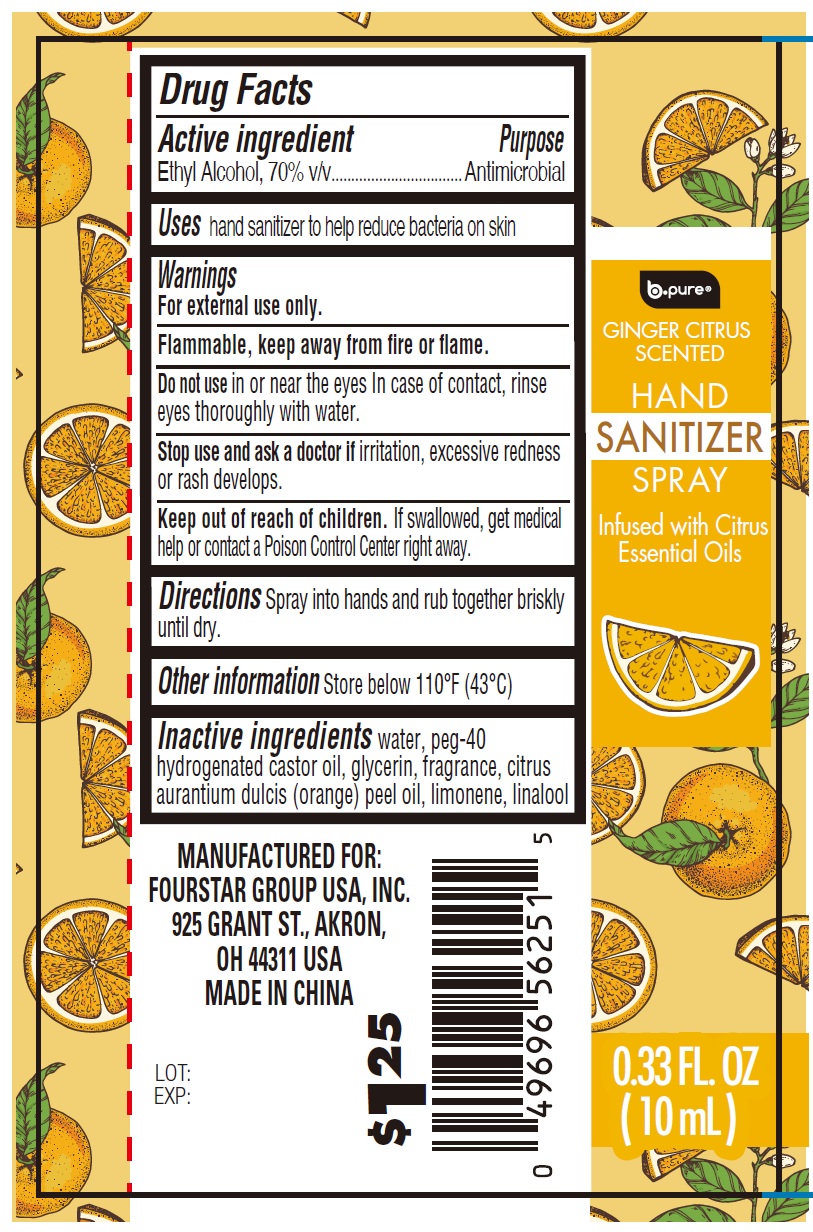 DRUG LABEL: B-Pure Hand Sanitizer Ginger Citrus Scented
NDC: 80684-160 | Form: LIQUID
Manufacturer: FOURSTAR GROUP USA, INC.
Category: otc | Type: HUMAN OTC DRUG LABEL
Date: 20250507

ACTIVE INGREDIENTS: ALCOHOL 70 mg/100 mL
INACTIVE INGREDIENTS: WATER; POLYOXYL 40 HYDROGENATED CASTOR OIL; GLYCERIN; ORANGE OIL, COLD PRESSED; LIMONENE, (+)-; LINALOOL, (+/-)-

B-Pure Hand Sanitizer Spray, Ginger Citrus Scented

Active ingredient

Ethyl Alcohol, 70% v/v

Purpose

Antimicrobial

Uses

hand sanitizer to help reduce bacteria on skin

Warnings

For external use only.

Flammable, keep away from fire or flame.

Do not use

in or near the eyes. In case of contact, rinse eyes thoroughly with water.

Stop use and ask a doctor if

irritation, excessive redness or rash develops.

Keep out of reach of children.

If swallowed, get medical help or contact a Poison Control Center right away

Directions

Spray into hands and rub together briskly until dry.

Other information

Store below 110°F (43°C)

Inactive ingredients

water, peg-40 hydrogenated castor oil, glycerin, fragrance, citrus aurantium dulcis (orange) peel oil, limonene, linalool